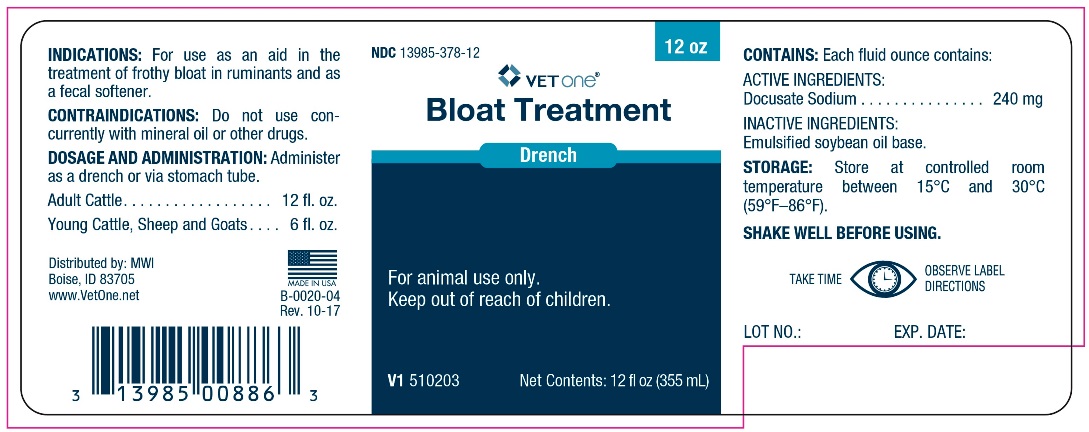 DRUG LABEL: BLOAT TREATMENT
NDC: 13985-378 | Form: EMULSION
Manufacturer: MWI/VetOne
Category: animal | Type: OTC ANIMAL DRUG LABEL
Date: 20180329

ACTIVE INGREDIENTS: DOCUSATE SODIUM 240 mg/29.57 mL

BLOAT TREATMENT

INDICATIONS AND USAGE

Drench

For animal use only.

Keep out of reach of children.

INDICATIONS

For use as an aid in the treatment of frothy bloat ruminants and as a fecal softener.

CONTRAINDICATIONS

Do not use concurrently with mineral oil or other drugs.

DOSAGE AND ADMINISTRATION

Administer as a drench or via stomach tube.

Adult Cattle................................. 12 fl. oz.

Young Cattle, Sheep and Goats .... 6 fl. oz.

CONTAINS

Each fl. oz. contains:

ACTIVE INGREDIENTS:
Docusate Sodium ................. 240 mg

INACTIVE INGREDIENTS:
Emulsified Soybean oil base.

STORAGE

Store at controlled room temperature between 15°C and 30°C (59°F-86°F)